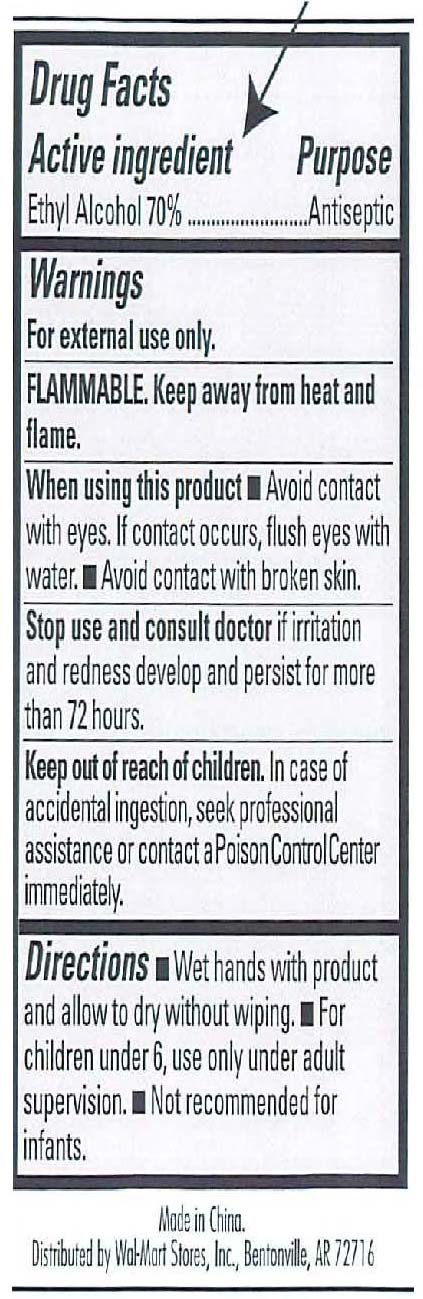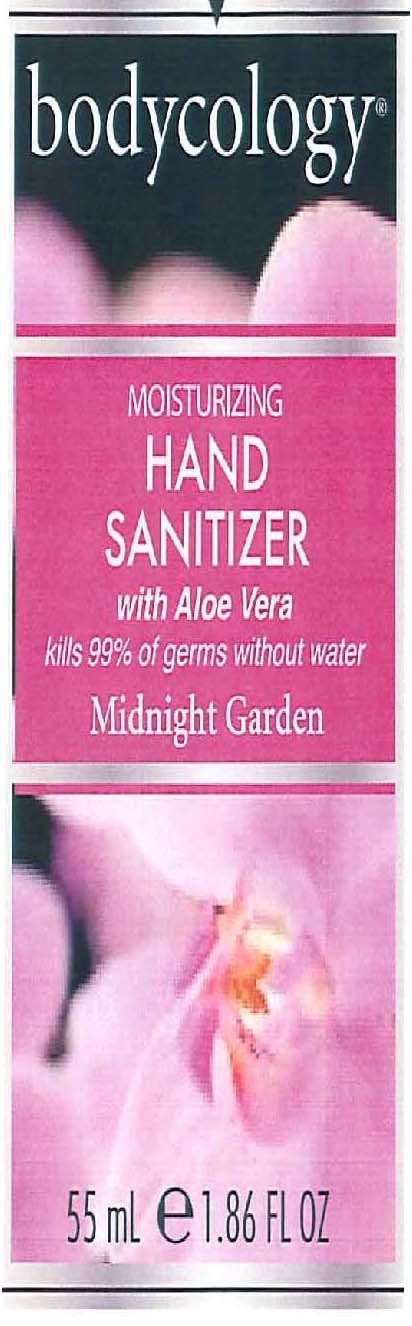 DRUG LABEL: Bodycology
NDC: 51706-304 | Form: GEL
Manufacturer: Landy International
Category: otc | Type: HUMAN OTC DRUG LABEL
Date: 20100713

ACTIVE INGREDIENTS: ALCOHOL 70 mL/100 mL

Moisturizing Hand Sanitizer Midnight Garden

Active Ingredient Purpose

Alcohol 70% Antiseptic

Warning:

-For external use only.

-Flammable. Keep away from heat and flame.

-When using this product, avoid contact with eyes. If contact occurs, flush eyes with water. Avoid contact with broken skin.

-Stop use and consult a doctor if irritation and redness develop and persist for more than 72 hours.

-Keep out of reach of children. In case of accidental ingestion, seek professional assistance or contact a Poison Control Center immediately.

Directions:

-Wet hands with product and allow to dry without wiping.

-For children under 6, use only under adult supervision. Not recommended for infants

PACKAGE LABEL

Bodycology
Moisturizing Hand Sanitizer
Midnight Gardenia
55 mL / 1.86 fl. oz.